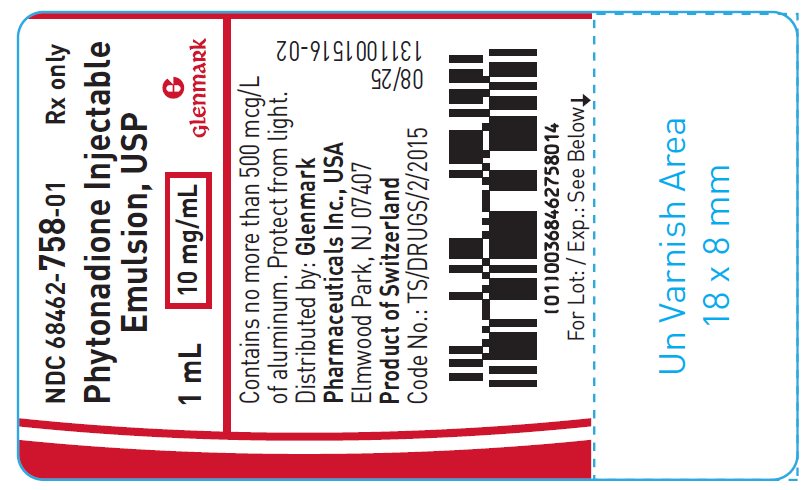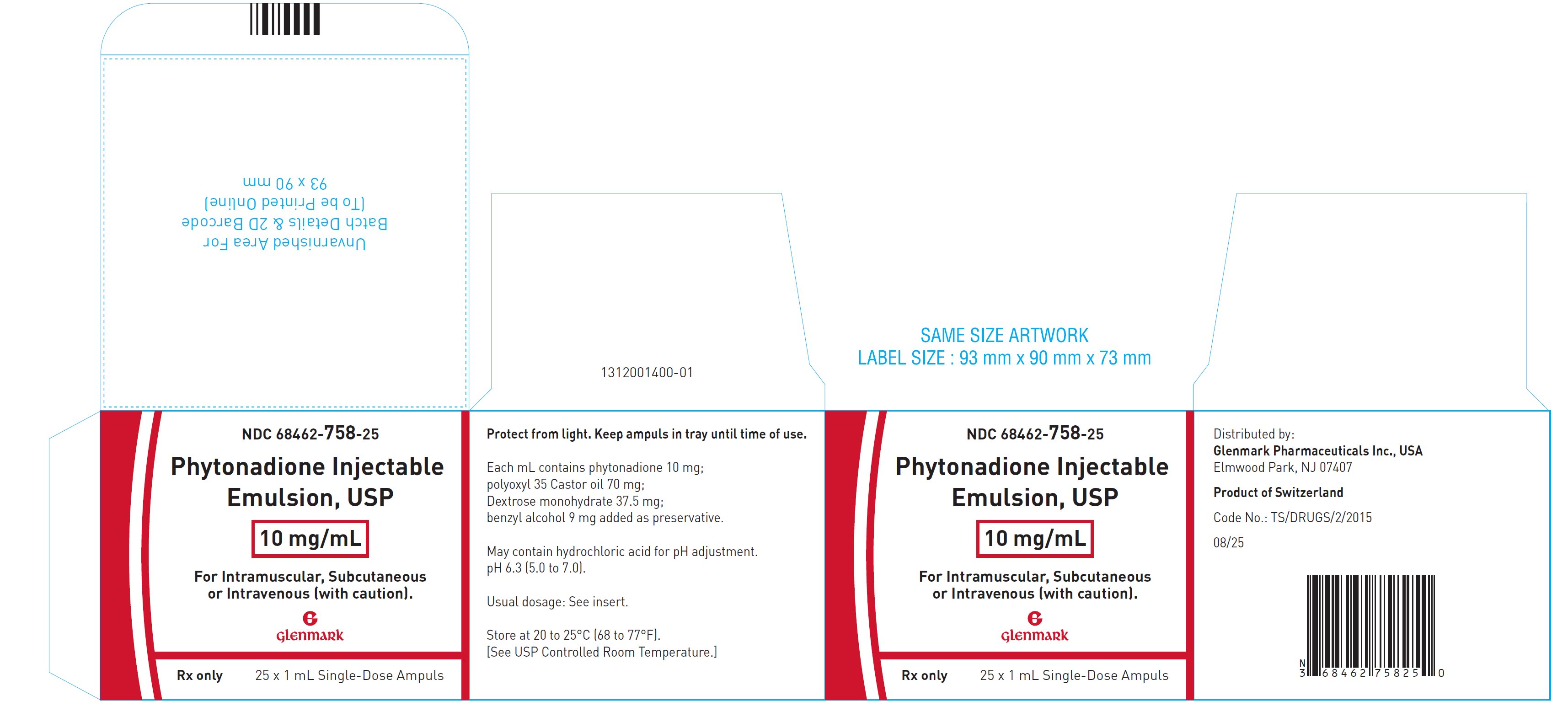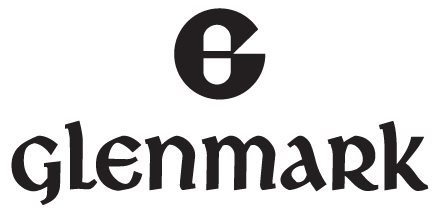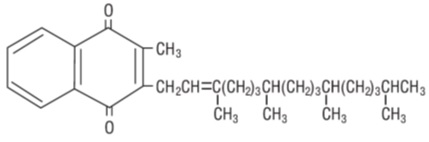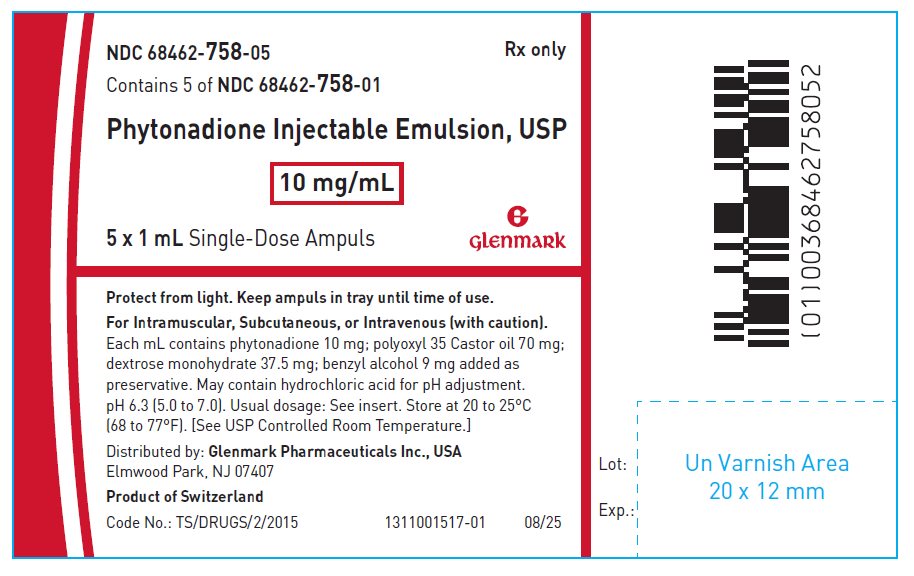 DRUG LABEL: Phytonadione
NDC: 68462-758 | Form: INJECTION, EMULSION
Manufacturer: GLENMARK PHARMACEUTICALS INC
Category: prescription | Type: HUMAN PRESCRIPTION DRUG LABEL
Date: 20251218

ACTIVE INGREDIENTS: PHYTONADIONE 10 mg/1 mL
INACTIVE INGREDIENTS: POLYOXYL 35 CASTOR OIL; DEXTROSE MONOHYDRATE; BENZYL ALCOHOL; HYDROCHLORIC ACID; WATER

Phytonadione Injectable Emulsion, USP
Aqueous Dispersion of Phytonadione
Ampul
Rx only
Protect from light.
Keep ampuls in tray until time of use.

WARNING — INTRAVENOUS AND INTRAMUSCULAR USE

Severe reactions, including fatalities, have occurred during and immediately after INTRAVENOUS injection of phytonadione, even when precautions have been taken to dilute the phytonadione and to avoid rapid infusion. Severe reactions, including fatalities, have also been reported following INTRAMUSCULAR administration.
Typically these severe reactions have resembled hypersensitivity or anaphylaxis, including shock and cardiac and/or respiratory arrest. Some patients have exhibited these severe reactions on receiving phytonadione for the first time.
Therefore the INTRAVENOUS and INTRAMUSCULAR routes should be restricted to those situations where the subcutaneous route is not feasible and the serious risk involved is considered justified.

DESCRIPTION

Phytonadione is a vitamin, which is a clear, yellow to amber, viscous, odorless or nearly odorless liquid. It is practically insoluble in water, sparingly soluble in ethanol and miscible with fatty oils. It has a molecular weight of 450.70.
Phytonadione is 2-Methyl-3’,7’,11’,15’-tetramethyl-hexadec-2’-en-1-yl-naphthalene-1,4 dione. Its empirical formula is C31H46O2 and its structural formula is:

Phytonadione Injectable Emulsion, USP is a yellow, sterile, nonpyrogenic aqueous dispersion available for injection by the intravenous, intramuscular and subcutaneous routes. Each milliliter contains phytonadione, USP 10 mg, polyoxyl 35 castor oil 70 mg, dextrose monohydrate 37.5 mg in water for injection; benzyl alcohol 9 mg added as preservative. May contain hydrochloric acid for pH adjustment. pH is 6.3 (5.0 to 7.0). Phytonadione is oxygen sensitive.

CLINICAL PHARMACOLOGY

Phytonadione Injectable Emulsion aqueous dispersion of Phytonadione for parenteral injection, possesses the same type and degree of activity as does naturally-occurring vitamin K, which is necessary for the production via the liver of active prothrombin (factor II), proconvertin (factor VII), plasma thromboplastin component (factor IX), and Stuart factor (factor X). The prothrombin test is sensitive to the levels of three of these four factors−II, VII, and X. Vitamin K is an essential cofactor for a microsomal enzyme that catalyzes the post-translational carboxylation of multiple, specific, peptide-bound glutamic acid residues in inactive hepatic precursors of factors II, VII, IX, and X. The resulting gamma-carboxy-glutamic acid residues convert the precursors into active coagulation factors that are subsequently secreted by liver cells into the blood.

Phytonadione is readily absorbed following intramuscular administration. After absorption, phytonadione is initially concentrated in the liver, but the concentration declines rapidly. Very little vitamin K accumulates in tissues. Little is known about the metabolic fate of vitamin K. Almost no free unmetabolized vitamin K appears in bile or urine.

In normal animals and humans, phytonadione is virtually devoid of pharmacodynamic activity. However, in animals and humans deficient in vitamin K, the pharmacological action of vitamin K is related to its normal physiological function, that is, to promote the hepatic biosynthesis of vitamin K dependent clotting factors.

The action of the aqueous dispersion, when administered intravenously, is generally detectable within an hour or two and hemorrhage is usually controlled within 3 to 6 hours. A normal prothrombin level may often be obtained in 12 to 14 hours.
In the prophylaxis and treatment of hemorrhagic disease of the newborn, phytonadione has demonstrated a greater margin of safety than that of the water-soluble vitamin K analogues.

INDICATIONS AND USAGE

Phytonadione Injectable Emulsion is indicated in the following coagulation disorders which are due to faulty formation of factors II, VII, IX and X when caused by vitamin K deficiency or interference with vitamin K activity.

Phytonadione Injectable Emulsion is indicated in:
• anticoagulant-induced prothrombin deficiency caused by coumarin or indanedione derivatives;
• prophylaxis and therapy of hemorrhagic disease of the newborn;
• hypoprothrombinemia due to antibacterial therapy;
• hypoprothrombinemia secondary to factors limiting absorption or synthesis of vitamin K, e.g., obstructive jaundice, biliary fistula, sprue, ulcerative colitis, celiac disease, intestinal resection, cystic fibrosis of the pancreas, and regional enteritis;
• other drug-induced hypoprothrombinemia where it is definitely shown that the result is due to interference with vitamin K metabolism, e.g., salicylates.

CONTRAINDICATION

Hypersensitivity to any component of this medication.

WARNINGS

Benzyl alcohol as a preservative in Bacteriostatic Sodium Chloride Injection has been associated with toxicity in newborns. Data are unavailable on the toxicity of other preservatives in this age group. There is no evidence to suggest that the small amount of benzyl alcohol contained in Phytonadione Injectable Emulsion, when used as recommended, is associated with toxicity.

An immediate coagulant effect should not be expected after administration of phytonadione. It takes a minimum of 1 to 2 hours for measurable improvement in the prothrombin time. Whole blood or component therapy may also be necessary if bleeding is severe.

Phytonadione will not counteract the anticoagulant action of heparin.

When Phytonadione is used to correct excessive anticoagulant-induced hypoprothrombinemia, anticoagulant therapy still being indicated, the patient is again faced with the clotting hazards existing prior to starting the anticoagulant therapy. Phytonadione is not a clotting agent, but overzealous therapy with Phytonadione may restore conditions which originally permitted thromboembolic phenomena. Dosage should be kept as low as possible, and prothrombin time should be checked regularly as clinical conditions indicate.

Repeated large doses of vitamin K are not warranted in liver disease if the response to initial use of the vitamin is unsatisfactory. Failure to respond to vitamin K may indicate that the condition being treated is inherently unresponsive to vitamin K.

Benzyl alcohol has been reported to be associated with a fatal "Gasping Syndrome" in premature infants.

WARNING: This product contains aluminum that may be toxic. Aluminum may reach toxic levels with prolonged parenteral administration if kidney function is impaired.

Premature neonates are particularly at risk because their kidneys are immature, and they required large amounts of calcium and phosphate solutions, which contain aluminum.

Research indicates that patients with impaired kidney function, including premature neonates, who receive parenteral levels of aluminum at greater than 4 to 5 mcg/kg/day accumulate aluminum at levels associated with central nervous system and bone toxicity. Tissue loading may occur at even lower rates of administration.

PRECAUTIONS

Drug Interactions
Temporary resistance to prothrombin-depressing anticoagulants may result, especially when larger doses of phytonadione are used. If relatively large doses have been employed, it may be necessary when reinstituting anticoagulant therapy to use somewhat larger doses of the prothrombin-depressing anticoagulant, or to use one which acts on a different principle, such as heparin sodium.

Laboratory Tests

Prothrombin time should be checked regularly as clinical conditions indicate.

Carcinogenesis, Mutagenesis, Impairment of Fertility
Studies of carcinogenicity, mutagenesis or impairment of fertility have not been conducted with Phytonadione Injectable Emulsion.

Pregnancy

Animal reproduction studies have not been conducted with phytonadione injectable emulsion. It is also not known whether phytonadione injectable emulsion can cause fetal harm when administered to a pregnant woman or can affect reproduction capacity. Phytonadione injectable emulsion should be given to a pregnant woman only if clearly needed.

Nursing Mothers

It is not known whether this drug is excreted in human milk. Because many drugs are excreted in human milk, caution should be exercised when phytonadione injectable emulsion is administered to a nursing woman.

Pediatric Use

Hemolysis, jaundice, and hyperbilirubinemia in neonates, particularly those that are premature, may be related to the dose of phytonadione injectable emulsion. Therefore, the recommended dose should not be exceeded (See ADVERSE REACTIONS and DOSAGE AND ADMINISTRATION).

ADVERSE REACTIONS

Deaths have occurred after intravenous and intramuscular administration. (See Box Warning.)

Transient "flushing sensations" and "peculiar" sensations of taste have been observed, as well as rare instances of dizziness, rapid and weak pulse, profuse sweating, brief hypotension, dyspnea, and cyanosis.

Pain, swelling, and tenderness at the injection site may occur.

The possibility of allergic sensitivity including an anaphylactoid reaction, should be kept in mind.

Infrequently, usually after repeated injection, erythematous, indurated, pruritic plaques have occurred; rarely, these have progressed to scleroderma-like lesions that have persisted for long periods. In other cases, these lesions have resembled erythema perstans.

Hyperbilirubinemia has been observed in the newborn following administration of phytonadione. This has occurred rarely and primarily with doses above those recommended (See PRECAUTIONS, Pediatric Use).

OVERDOSAGE

The intravenous LD50 of Phytonadione Injectable Emulsion in the mouse is 41.5 and 52 mL/kg for the 0.2% and 1% concentrations, respectively.

DOSAGE AND ADMINISTRATION

Whenever possible, Phytonadione Injectable Emulsion, USP should be given by the subcutaneous route (See Box Warning). When intravenous administration is considered unavoidable, the drug should be injected very slowly, not exceeding 1 mg per minute.

Protect from light at all times.

Parenteral drug products should be inspected visually for particulate matter and discoloration prior to administration, whenever solution and container permit.

Directions for Dilution

Phytonadione injectable emulsion, USP may be diluted with 0.9% Sodium Chloride Injection, 5% Dextrose Injection, or 5% Dextrose and Sodium Chloride Injection. Benzyl alcohol as a preservative has been associated with toxicity in newborns. Therefore, all of the above diluents should be preservative-free (See WARNINGS). Other diluents should not be used. When dilutions are indicated, administration should be started immediately after mixture with the diluent, and unused portions of the dilution should be discarded, as well as unused contents of the ampul.

Prophylaxis of Hemorrhagic Disease of the Newborn

The American Academy of Pediatrics recommends that Phytonadione be given to the newborn. A single intramuscular dose of phytonadione injectable emulsion, USP 0.5 to 1 mg within one hour of birth is recommended.

Treatment of Hemorrhagic Disease of the Newborn
Empiric administration of Phytonadione should not replace proper laboratory evaluation of the coagulation mechanism. A prompt response (shortening of the prothrombin time in 2 to 4 hours) following administration of Phytonadione is usually diagnostic of hemorrhagic disease of the newborn, and failure to respond indicates another diagnosis or coagulation disorder.

Phytonadione injectable emulsion, USP 1 mg should be given either subcutaneously or intramuscularly. Higher doses may be necessary if the mother has been receiving oral anticoagulants.

Whole blood or component therapy may be indicated if bleeding is excessive. This therapy, however, does not correct the underlying disorder and phytonadione injectable emulsion, USP should be given concurrently.

Anticoagulant-Induced Prothrombin Deficiency in Adults
To correct excessively prolonged prothrombin time caused by oral anticoagulant therapy—2.5 to 10 mg or up to 25 mg initially is recommended. In rare instances 50 mg may be required. Frequency and amount of subsequent doses should be determined by prothrombin time response or clinical condition (See WARNINGS). If in 6 to 8 hours after parenteral administration the prothrombin time has not been shortened satisfactorily, the dose should be repeated.

Phytonadione Injectable Emulsion, USP Summary of Dosage Guidelines (See circular text for details)

Newborns | Dosage
Hemorrhagic Disease of the Newborn Prophylaxis | 0.5 to 1 mg IM within 1 hour of birth
Treatment | 1 mg SC or IM (Higher doses may be necessary if the mother has been receiving oral anticoagulants)
Adults | Initial Dosage
Anticoagulant-Induced Prothrombin Deficiency (caused by coumarin or indanedione derivatives) | 2.5 mg to 10 mg or up to 25 mg (rarely 50 mg)
Hypoprothrombinemia Due to other causes (Antibiotics; Salicylates or other drugs; Factors limiting absorption or synthesis) | 2.5 mg to 25 mg or more (rarely up to 50 mg)

In the event of shock or excessive blood loss, the use of whole blood or component therapy is indicated.

Hypoprothrombinemia Due to Other Causes in Adults

A dosage of 2.5 to 25 mg or more (rarely up to 50 mg) is recommended, the amount and route of administration depending upon the severity of the condition and response obtained.
If possible, discontinuation or reduction of the dosage of drugs interfering with coagulation mechanisms (such as salicylates; antibiotics) is suggested as an alternative to administering concurrent phytonadione injectable emulsion, USP. The severity of the coagulation disorder should determine whether the immediate administration of phytonadione injectable emulsion, USP is required in addition to discontinuation or reduction of interfering drugs.

HOW SUPPLIED

Phytonadione Injectable Emulsion, USP is supplied as follows:

Unit of Sale | Concentration
NDC 68462-758-25 25 ampuls (Bundle of 5 clamcells, each clamcell containing 5 single-dose ampuls) | 10 mg/mL

Store at 20 to 25°C (68 to 77°F). [See USP Controlled Room Temperature.]

Protect from light. Keep ampuls in tray until time of use.

Distributed by:

Glenmark Pharmaceuticals Inc., USA

Elmwood Park, NJ 07407

August 2025

PACKAGE LABEL.PRINCIPAL DISPLAY PANEL

Outer carton Label

NDC 68462-758-25

Phytonadione Injectable
Emulsion, USP
10 mg/mL
For Intramuscular, Subcutaneous
or Intravenous (with caution).
Rx only 25 x 1 mL Single-Dose Ampuls

Package/Label Display Panel

Tray Label

NDC 68462-758-05 Rx only
Contains 5 of NDC 68462-758-01
Phytonadione Injectable Emulsion, USP
10 mg/mL

5 x 1 mL Single-Dose Ampuls

Ampul Label

NDC 68462-758-01 Rx only
Phytonadione Injectable
Emulsion, USP
10 mg/mL

1 mL